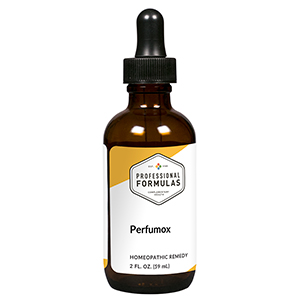 DRUG LABEL: Perfumox
NDC: 63083-6028 | Form: LIQUID
Manufacturer: Professional Complementary Health Formulas
Category: homeopathic | Type: HUMAN OTC DRUG LABEL
Date: 20190815

ACTIVE INGREDIENTS: SCHOENOCAULON OFFICINALE SEED 6 [hp_X]/59 mL; STRYCHNOS NUX-VOMICA SEED 8 [hp_X]/59 mL; CANANGA ODORATA LEAF OIL 15 [hp_X]/59 mL; ACETONE 60 [hp_X]/59 mL; PHOSPHORUS 12 [hp_X]/59 mL; AMARYLLIS BELLADONNA WHOLE 30 [hp_X]/59 mL; CINNAMIC ACID 30 [hp_X]/59 mL; SULFUR IODIDE 30 [hp_X]/59 mL; ACETALDEHYDE 30 [hp_X]/59 mL; COLCHICUM AUTUMNALE BULB 60 [hp_X]/59 mL; BENZENE 60 [hp_X]/59 mL; EUGENOL 60 [hp_X]/59 mL; INDOLE-3-CARBINOL 60 [hp_X]/59 mL; CITRUS AURANTIUM FLOWER OIL 60 [hp_X]/59 mL; LIQUID PETROLEUM 100 [hp_X]/59 mL
INACTIVE INGREDIENTS: ALCOHOL; WATER

X28

ACTIVE INGREDIENTS

Sabadilla 6X, 12X
Nux vomica 8X
Ylang ylang 15X
Acetonum 60X, 100X, 200X
Phosphorus 12C
Belladonna 30C
Cinnamic acid 30C
Sulphur iodatum 30C
Acetaldehyde 30C, 60C, 100C
Colchicum autumnale 60C
Benzinum 60C, 100C, 200C
Eugenol 60C, 100C, 200C
Indolum 60C, 100C, 200C
Mixed perfumes 60C, 100C, 200C
Petroleum 100C

QUESTIONS

Professional Formulas

PO Box 2034 Lake Oswego, OR 97035

INDICATIONS

For the temporary relief of occasional headache, difficulty breathing, runny or stuffy nose, sneezing, or red, itchy skin due to sensitivity to or exposure to perfumes or fragrances.*

PURPOSE

*Claims based on traditional homeopathic practice, not accepted medical evidence. Not FDA evaluated.

WARNINGS

In case of overdose, get medical help or contact a poison control center right away.

Keep out of the reach of children.

PREGNANCY OR BREAST FEEDING

If pregnant or breastfeeding, ask a healthcare professional before use.

DIRECTIONS

Place drops under tongue 30 minutes before/after meals. Adults and children 12 years and over: Take 10 drops up to 3 times per day. Consult a physician for use in children under 12 years of age.

OTHER INFORMATION

Tamper resistant. If seal is broken, do not use. After opening, close container tightly and store at room temperature away from heat.

INACTIVE INGREDIENTS

20% ethanol, purified water.

LABEL

Est 1985

Professional Formulas

Complementary Health

Perfumox

Homeopathic Remedy

2 FL. OZ. (59 mL)